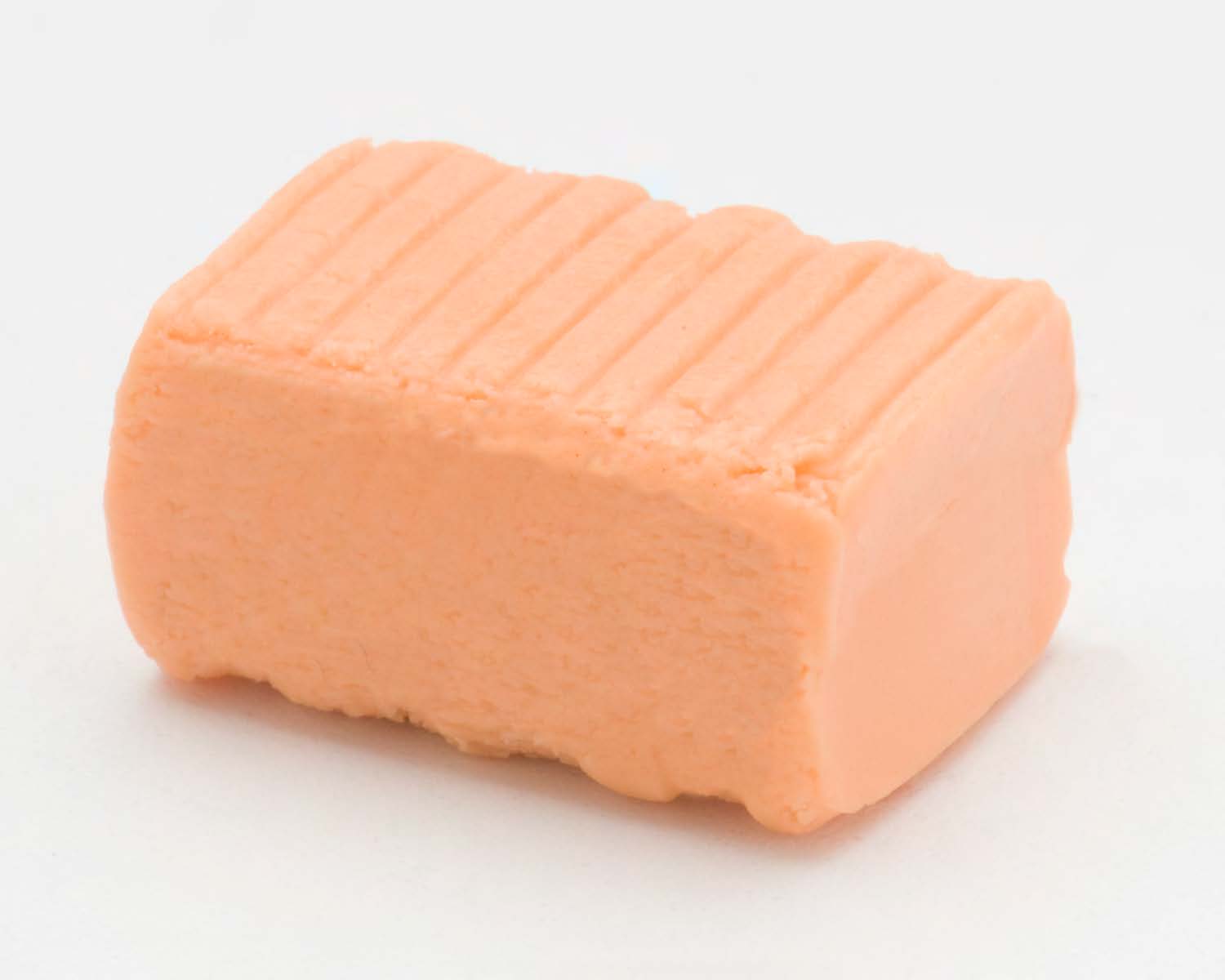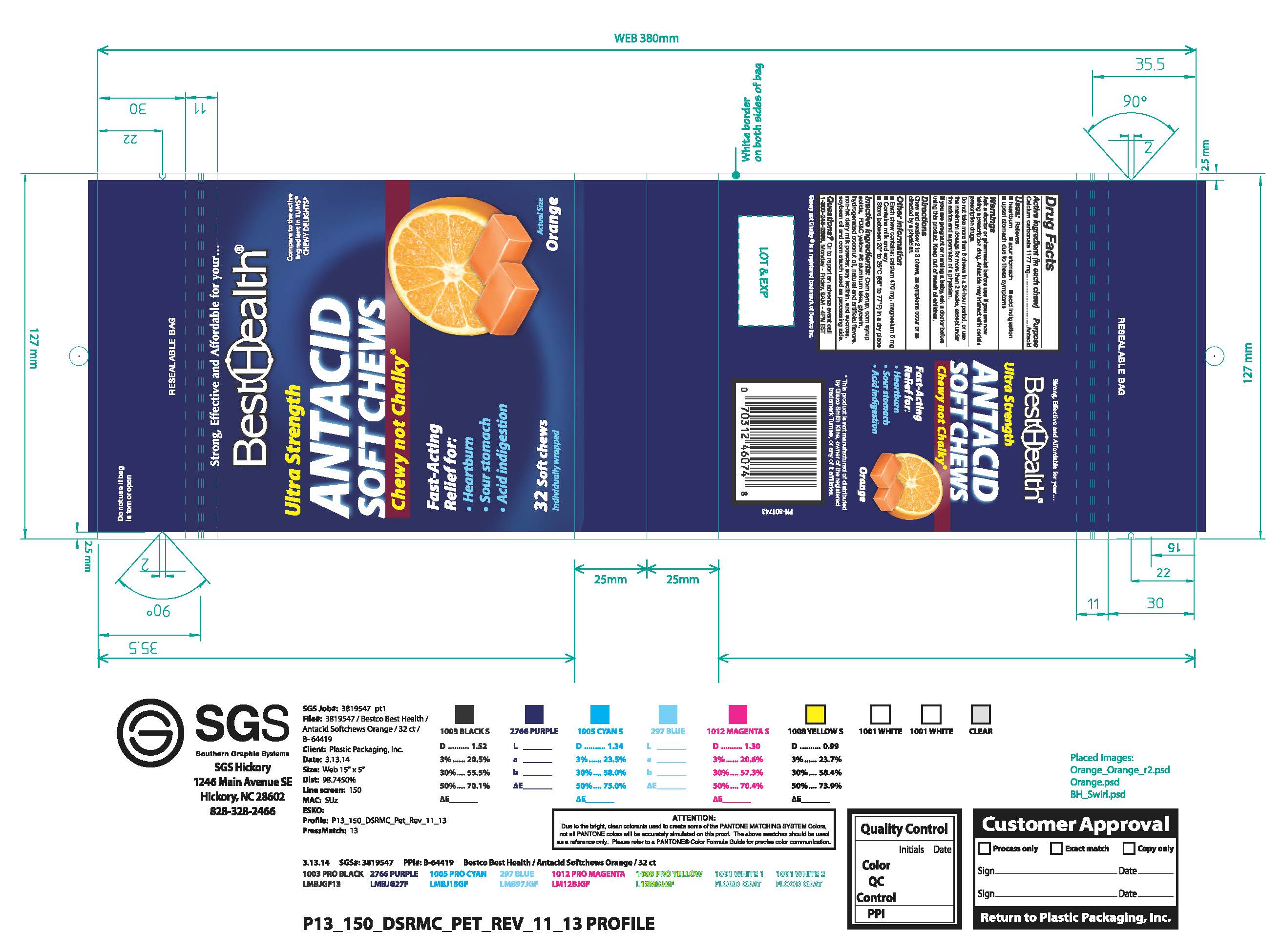 DRUG LABEL: Orange Antacid Softchew
NDC: 52642-021 | Form: TABLET, CHEWABLE
Manufacturer: BestCo Inc.
Category: otc | Type: HUMAN OTC DRUG LABEL
Date: 20140314

ACTIVE INGREDIENTS: CALCIUM CARBONATE 1177 mg/1 1
INACTIVE INGREDIENTS: SUCROSE

Calcium carbonate 1177 mg

Active ingredient (in each chew)

Calcium Carbonate 1177 mg

Purpose

Antacid

INDICATIONS AND USAGE

Uses: relieves

heartburn

sour stomach

acid indigestion

upset stomach due to these symptoms

Warnings

Ask a doctor or pharmacist before use if you are now taking a prescription drug. Antacids may interact with certain perscription drugs.

Do not take more than 6 chews in a 34-hour period, or use the maximum dosage for more than 2 weeks, except under the advice and supervision of a physician.

PREGNANCY OR BREAST FEEDING

If you ae pregnant or nursing a baby, ask a doctor before using this product.

Keep out of reach of children.

Directions

Chew and swallow 2 to 3 chews, as symptoms occur or as directed by a physician.

Other information

Each chew contains: calcium 470 mg, mangesium 5mg

Contains milk and soy

Store between 20° to 25ºC (68º to 77ºF) in a dry place

INACTIVE INGREDIENT

inactive ingredients: Corn syrup, corn syrup solids, FD&C yellow #6 aluminum lake, glycerin, hydrogenated coconut oil, natural and artificial flavors, non-fat dairy milk powder, soy lecithin, and sucrose. Soybean oil and corn starch used as processing aids.

QUESTIONS

Questions? Or to report an adverse event call 1-800-245-2898, Monday - Friday, 8AM -4PM EST